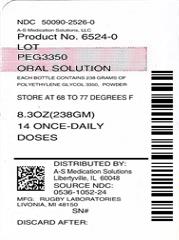 DRUG LABEL: PEG 3350
NDC: 50090-2526 | Form: POWDER
Manufacturer: A-S Medication Solutions
Category: otc | Type: HUMAN OTC DRUG LABEL
Date: 20180215

ACTIVE INGREDIENTS: POLYETHYLENE GLYCOL 3350 17 g/17 g

Drug Facts

Inactive Ingredients

Inactive Ingredients none

Active Ingredient

Active Ingredient (in each dose)

Polyethylene Glycol 3350, 17 g (cap filled to line)

Purpose

Osmotic Laxative

Warnings

Allergy Alert: Do not use if you are allergic to polyethylene glycol

Do not use if you have kidney disease, except under the advice and supervision of a doctor

When using this product, you may have loose, watery, more frequent bowel movements

Ask Doctor

Ask a doctor before use if you have

-nausea, vomiting or abdominal pain

-a sudden change in bowel habits that lasts over 2 weeks

-irritable bowel syndrome

Ask a doctor or pharmacist before use if you are taking a prescription drug

Stop Use

Stop use and ask a doctor if

- you have rectal bleeding or your nausea, bloating, cramping or abdominal pain gets worse.These may be sogns of a serious condition.

- you get diarrhea

- you need to use a laxative for longer than 1 week

- side effects occur

Keep out of reach of children. In case of overdose, get medical help or contact a POISON CONTROL CENTER right away.

Pregnancy Warning

If pregnant or breast-feeding, ask a health professional before use.

Dosage and Administration

Directions

-do not take more than directed unless advised by your doctor

-the bottle top is a measuring cap marked to contain 17 grams of powder when filled to the indicated line

-adults and children 17 years of age and older:

-fill to top of line in cap which is marked to indicate the correct dose (17 g)

-stir and dissolve in any 4 to 8 ounces of beverage (cold, hot or room temperature) and then drink

-use once a day

-use no more than 7 days

-Children 16 years of age or under: ask a doctor

Questions?

Questions or comments?

1-800-645-2158

Indications and Usage

Use

-relieves occasional constipation (irregularity)

-generally produces a bowel movement in 1 to 3 days

HOW SUPPLIED

Product: 50090-2526

NDC: 50090-2526-0 238 g in a BOTTLE